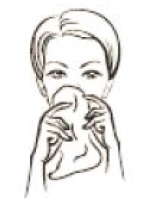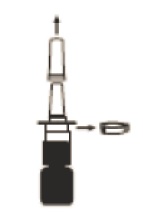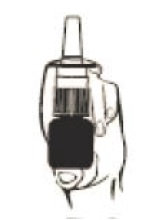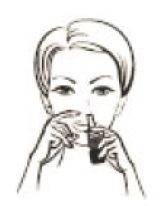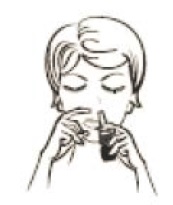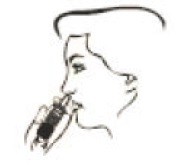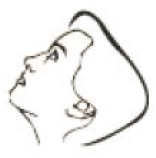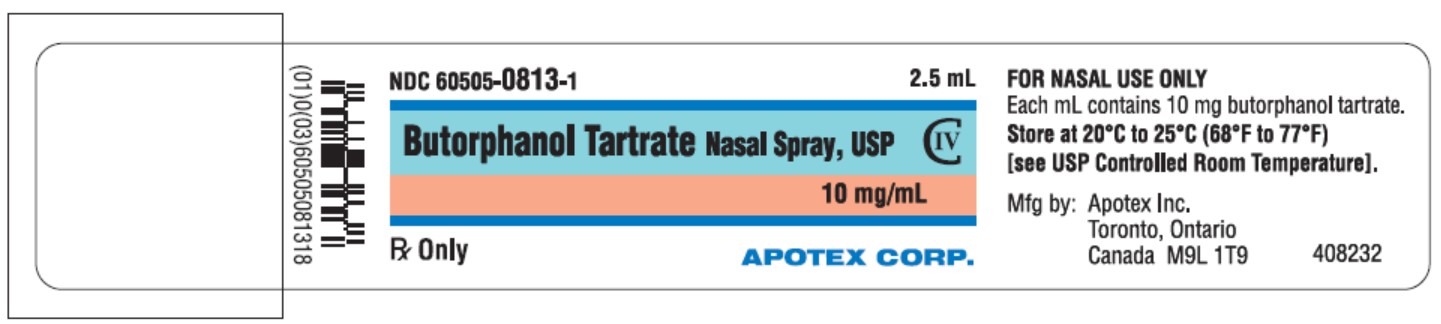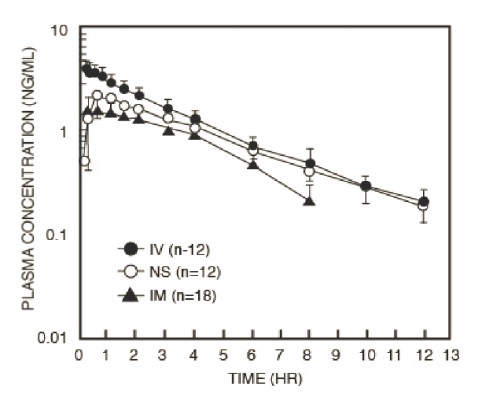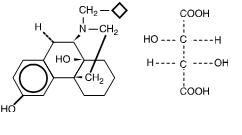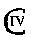 DRUG LABEL: Butorphanol Tartrate
NDC: 60505-0813 | Form: SPRAY
Manufacturer: Apotex Corp.
Category: prescription | Type: HUMAN PRESCRIPTION DRUG LABEL
Date: 20251203
DEA Schedule: CIV

ACTIVE INGREDIENTS: BUTORPHANOL TARTRATE 10 mg/1 mL
INACTIVE INGREDIENTS: SODIUM CHLORIDE; CITRIC ACID MONOHYDRATE; BENZETHONIUM CHLORIDE; WATER; SODIUM HYDROXIDE; HYDROCHLORIC ACID

Prescribing Information
Rx Only
Butorphanol Tartrate Nasal Spray USP, 10 mg/mL CIV

WARNING: SERIOUS AND LIFE-THREATENING RISKS FROM USE OF BUTORPHANOL TARTRATE NASAL SPRAY

Addiction, Abuse, and Misuse
Because the use of butorphanol tartrate nasal spray exposes patients and other users to the risks of opioid addiction, abuse, and misuse, which can lead to overdose and death, assess each patient’s risk prior to prescribing and reassess all patients regularly for the development of these behaviors and conditions [see WARNINGS].

Life-Threatening Respiratory Depression

Serious, life-threatening, or fatal respiratory depression may occur with use of butorphanol tartrate nasal spray, especially during initiation or following a dosage increase. To reduce the risk of respiratory depression, proper dosing and titration of butorphanol tartrate nasal spray are essential [see WARNINGS].

Accidental Exposure

Accidental exposure of even one dose of butorphanol tartrate nasal spray, especially in children, can result in a fatal overdose of butorphanol tartrate [see WARNINGS].

Risks From Concomitant Use With Benzodiazepines Or Other CNS Depressants
Concomitant use of opioids with benzodiazepines or other central nervous system (CNS) depressants, including alcohol, may result in profound sedation, respiratory depression, coma, and death. Reserve concomitant prescribing of butorphanol tartrate nasal spray and benzodiazepines or other CNS depressants for use in patients for whom alternative treatment options are inadequate [see WARNINGS, PRECAUTIONS; Drug Interactions].

Neonatal Opioid Withdrawal Syndrome (NOWS)

Advise pregnant women using opioids for an extended period of time of the risk of Neonatal Opioid Withdrawal Syndrome, which may be life-threatening if not recognized and treated. Ensure that management by neonatology experts will be available at delivery [see WARNINGS].

Opioid Analgesic Risk Evaluation and Mitigation Strategy (REMS):

Healthcare providers are strongly encouraged to complete a REMS-compliant education program and to counsel patients and caregivers on serious risks, safe use, and the importance of reading the Medication Guide with each prescription [see WARNINGS].

Cytochrome P450 3A4 Interaction

The concomitant use of butorphanol tartrate nasal spray with all cytochrome P450 3A4 inhibitors may result in an increase in butorphanol plasma concentrations, which could increase or prolong adverse reactions and may cause potentially fatal respiratory depression. In addition, discontinuation of a concomitantly used cytochrome P450 3A4 inducer may result in an increase in butorphanol plasma concentration. Monitor patients receiving butorphanol tartrate nasal spray and any CYP3A4 inhibitor or inducer [see CLINICAL PHARMACOLOGY, WARNINGS, PRECAUTIONS; Drug Interactions].

DESCRIPTION

Butorphanol tartrate is a synthetically derived opioid agonist-antagonist analgesic of the phenanthrene series. The chemical name is (-)-17-(cyclobutylmethyl)morphinan-3,14-diol[S-(R*,R*)]-2,3-dihydroxybutanedioate (1:1) (salt). The molecular formula is C21H29NO2•C4H6O6, which corresponds to a molecular weight of 477.55 g/mol and the following structural formula:

Butorphanol tartrate is a white crystalline substance. The dose is expressed as the tartrate salt. One milligram of the salt is equivalent to 0.68 mg of the free base. The n-octanol/aqueous buffer partition coefficient of butorphanol is 180:1 at pH 7.5.

Butorphanol tartrate nasal spray, USP is an aqueous solution of butorphanol tartrate for administration as a metered spray to the nasal mucosa. Each bottle of butorphanol tartrate nasal spray, USP contains 2.5 mL of a 10 mg/mL solution of butorphanol tartrate with sodium chloride, citric acid, and benzethonium chloride in purified water with sodium hydroxide and/or hydrochloric acid added to adjust the pH to 5. The pump reservoir must be fully primed [see PATIENT INSTRUCTIONS] prior to initial use. After initial priming each metered spray delivers an average of 1 mg of butorphanol tartrate and the 2.5 mL bottle will deliver an average of 14 to 15 doses of butorphanol tartrate nasal spray, USP. If not used for 48 hours or longer, the unit must be reprimed [see PATIENT INSTRUCTIONS]. With intermittent use requiring repriming before each dose, the 2.5 mL bottle will deliver an average of 8 to 10 doses of butorphanol tartrate nasal spray, USP depending on how much repriming is necessary.

CLINICAL PHARMACOLOGY

Mechanism of Action

Butorphanol is a partial opioid agonist at the mu opioid receptor and a full agonist at the kappa opioid receptor. The principal therapeutic action of butorphanol is analgesia. Clinically, dosage is titrated to provide adequate analgesia and may be limited by adverse reactions, including respiratory and CNS depression.

The precise mechanism of the analgesic action is unknown. However, specific CNS opioid receptors for endogenous compounds with opioid-like activity have been identified throughout the brain and spinal cord and are thought to play a role in the analgesic effects of this drug.

Pharmacodynamics

The analgesic effect of butorphanol is influenced by the route of administration. Onset of analgesia is within 15 minutes for the nasal administration doses. Peak analgesic activity occurs within 1 to 2 hours following nasal spray administration.

The duration of analgesia varies depending on the pain model as well as the route of administration. Compared to the injectable form and other drugs in this class, butorphanol tartrate nasal spray has a longer duration of action (4 to 5 hours) [see CLINICAL PHARMACOLOGY; Clinical Trials].

Effects on the Central Nervous System

Butorphanol produces respiratory depression by direct action on brain stem respiratory centers. The respiratory depression involves a reduction in the responsiveness of the brain stem respiratory centers to both increases in carbon dioxide tension and electrical stimulation.

In human studies involving individuals without significant respiratory dysfunction, 2 mg of butorphanol IV and 10 mg of morphine sulfate IV depressed respiration to a comparable degree. At higher doses, the magnitude of respiratory depression with butorphanol is not appreciably increased; however, the duration of respiratory depression is longer. Respiratory depression noted after administration of butorphanol to humans by any route is reversed by treatment with naloxone, a specific opioid antagonist [see OVERDOSAGE].

Butorphanol, like other mixed agonist-antagonists with a high affinity for the κ-receptor, may produce unpleasant psychotomimetic effects in some individuals.

Nausea and/or vomiting may be produced by doses of 1 mg or more administered by any route.

In human studies of butorphanol [see CLINICAL PHARMACOLOGY; Clinical Trials], sedation is commonly noted at doses of 0.5 mg or more. Narcosis is produced by 10 to 12 mg doses of butorphanol administered over 10 to 15 minutes intravenously.

Butorphanol causes miosis, even in total darkness. Pinpoint pupils are a sign of opioid overdose but are not pathognomonic (e.g., pontine lesions of hemorrhagic or ischemic origins may produce similar findings). Marked mydriasis rather than miosis may be seen due to hypoxia in overdose situations.

Effects on the Gastrointestinal Tract and Other Smooth Muscle

Butorphanol causes a reduction in motility associated with an increase in smooth muscle tone in the antrum of the stomach and duodenum. Digestion of food in the small intestine is delayed and propulsive contractions are decreased. Propulsive peristaltic waves in the colon are decreased, while tone may be increased to the point of spasm, resulting in constipation. Other opioid-induced effects may include a reduction in biliary and pancreatic secretions, spasm of sphincter of Oddi, transient elevations in serum amylase, and opioid-induced esophageal dysfunction (OIED).

Effects on the Cardiovascular System

Hemodynamic changes noted during cardiac catheterization in patients receiving single 0.025 mg/kg intravenous doses of butorphanol have included increases in pulmonary artery pressure, wedge pressure and vascular resistance, increases in left ventricular end diastolic pressure, and in systemic arterial pressure.

Effects on the Endocrine System

Opioids inhibit the secretion of adrenocorticotropic hormone (ACTH), cortisol, and luteinizing hormone (LH) in humans [see ADVERSE REACTIONS]. They also stimulate prolactin, growth hormone (GH) secretion, and pancreatic secretion of insulin and glucagon.

Use of opioids for an extended period of time may influence the hypothalamic-pituitary-gonadal axis, leading to androgen deficiency that may manifest as low libido, impotence, erectile dysfunction, amenorrhea, or infertility. The causal role of opioids in the clinical syndrome of hypogonadism is unknown because the various medical, physical, lifestyle, and psychological stressors that may influence gonadal hormone levels have not been adequately controlled for in studies conducted to date [see ADVERSE REACTIONS].

Effects on the Immune System

Opioids have been shown to have a variety of effects on components of the immune system. The clinical significance of these findings is unknown. Overall, the effects of opioids appear to be modestly immunosuppressive.

Concentration–Efficacy Relationships

The minimum effective analgesic concentration will vary widely among patients, especially among patients who have been previously treated with opioid agonists. The minimum effective analgesic concentration of butorphanol for any individual patient may increase over time due to an increase in pain, the development of a new pain syndrome, and/or the development of analgesic tolerance [see DOSAGE AND ADMINISTRATION].

Concentration–Adverse Reaction Relationships

There is a relationship between increasing butorphanol plasma concentration and increasing frequency of dose-related opioid adverse reactions such as nausea, vomiting, CNS effects, and respiratory depression. In opioid-tolerant patients, the situation may be altered by the development of tolerance to opioid-related adverse reactions [see DOSAGE AND ADMINISTRATION].

Pharmacokinetics

After nasal administration, mean peak blood levels of 0.9 to 1.04 ng/mL occur at 30 to 60 minutes after a 1 mg dose (see Table 1). The absolute bioavailability of butorphanol tartrate nasal spray is 60 to 70% and is unchanged in patients with allergic rhinitis. In patients using a nasal vasoconstrictor (oxymetazoline) the fraction of the dose absorbed was unchanged, but the rate of absorption was slowed. The peak plasma concentrations were approximately half those achieved in the absence of the vasoconstrictor.

Following its initial absorption/distribution phase, the single dose pharmacokinetics of butorphanol by the intravenous, intramuscular, and nasal routes of administration are similar (see Figure 1).

Figure 1: Butorphanol Plasma Levels After IV, IM and Nasal Spray Administration of 2 mg Dose

Serum protein binding is independent of concentration over the range achieved in clinical practice (up to 7 ng/mL) with a bound fraction of approximately 80%.

The volume of distribution of butorphanol varies from 305 to 901 liters and total body clearance from 52 to 154 liters/hr (see Table 1).

Table 1: Mean Pharmacokinetic Parameters of Butorphanol in Young and Elderly Subjects^1
 | Intravenous |  | Nasal
Parameters | Young | Elderly | Young | Elderly
Tmax^2 (hr) |  |  | 0.62 (0.32)^3 (0.15 to 1.50)^4 | 1.03 (0.74) (0.25 to 3.00)
Cmax^5 (ng/mL) |  |  | 1.04 (0.40) (0.35 to 1.97) | 0.90 (0.57) (0.10 to 2.68)
AUC (inf)^6 (hr·ng/mL) | 7.24 (1.57) (4.40 to 9.77) | 8.71 (2.02) (4.76 to 13.03) | 4.93 (1.24) (2.16 to 7.27) | 5.24 (2.27) (0.30 to 10.34)
Half-life (hr) | 4.56 (1.67) (2.06 to 8.70) | 5.61 (1.36) (3.25 to 8.79) | 4.74 (1.57) (2.89 to 8.79) | 6.56 (1.51) (3.75 to 9.17)
Absolute Bioavailability (%) |  |  | 69 (16) (44 to 113) | 61 (25) (3 to 121)
Volume of Distribution^7 (L) | 487 (155) (305 to 901) | 552 (124) (305 to 737)
Total Body Clearance (L/hr) | 99 (23) (70 to 154) | 82 (21) (52 to 143)

^1. Young subjects (n=24) are from 20 to 40 years old and elderly (n=24) are greater than 65 years of age.

^2. Time to peak plasma concentration.

^3. Mean (1 S.D.)

^4. (range of observed values)

^5. Peak plasma concentration normalized to 1 mg dose.

^6. Area under the plasma concentration-time curve after a 1 mg dose.

^7. Derived from IV data.

Dose proportionality for butorphanol tartrate nasal spray has been determined at steady state in doses up to 4 mg at 6-hour intervals. Steady state is achieved within 2 days. The mean peak plasma concentration at steady state was 1.8-fold (maximal 3-fold) following a single dose.

The drug is transported across the blood brain and placental barriers and into human milk [see PRECAUTIONS: Labor and Delivery and Nursing Mothers].

Butorphanol is extensively metabolized in the liver. Metabolism is qualitatively and quantitatively similar following intravenous, intramuscular, or nasal administration. Oral bioavailability is only 5 to 17% because of extensive first pass metabolism of butorphanol.

The major metabolite of butorphanol is hydroxybutorphanol, while norbutorphanol is produced in small amounts. Both have been detected in plasma following administration of butorphanol, with norbutorphanol present at trace levels at most time points. The elimination half-life of hydroxybutorphanol is about 18 hours and, as a consequence, considerable accumulation (~5-fold) occurs when butorphanol is dosed to steady state (1 mg transnasally q6h for 5 days).

Elimination occurs by urine and fecal excretion. When ^3H labelled butorphanol is administered to normal subjects, most (70 to 80%) of the dose is recovered in the urine, while approximately 15% is recovered in the feces.

About 5% of the dose is recovered in the urine as butorphanol. Forty-nine percent is eliminated in the urine as hydroxybutorphanol. Less than 5% is excreted in the urine as norbutorphanol.

Butorphanol pharmacokinetics in the elderly differ from younger patients (see Table 1). The mean absolute bioavailability of butorphanol tartrate nasal spray in elderly women (48%) was less than that in elderly men (75%), young men (68%), or young women (70%). Elimination half-life is increased in the elderly (6.6 hours as opposed to 4.7 hours in younger subjects).

In renally impaired patients with creatinine clearances <30 mL/min, the elimination half-life was approximately doubled, and the total body clearance was approximately one half (10.5 hours [clearance 150 L/h] as compared to 5.8 hours [clearance 260 L/h] in healthy subjects). No effect on Cmax or Tmax was observed after a single dose.

After intravenous administration to patients with hepatic impairment, the elimination half-life of butorphanol was approximately tripled and total body clearance was approximately one half (half-life 16.8 hours, clearance 92 L/h) compared to healthy subjects (half-life 4.8 hours, clearance 175 L/h). The exposure of hepatically impaired patients to butorphanol was significantly greater (about 2-fold) than that in healthy subjects. Similar results were seen after nasal administration. No effect on Cmax or Tmax was observed after a single intranasal dose.

For further recommendations refer to PRECAUTIONS: Hepatic and Renal Disease, Drug Interactions, and Geriatric Use sections and to the DOSAGE AND ADMINISTRATION section below.

Drug Interactions

Sumatriptan

In healthy volunteers, the pharmacokinetics of a 1 mg dose of butorphanol administered as butorphanol tartrate nasal spray were not affected by the coadministration of a single 6 mg subcutaneous dose of sumatriptan. However, in another study in healthy volunteers, the pharmacokinetics of butorphanol were significantly altered (29% decrease in AUC and 38% decreases in Cmax) when a 1 mg dose of butorphanol tartrate nasal spray was administered 1 minute after a 20 mg dose of sumatriptan nasal spray. (The two drugs were administered in opposite nostrils.) When the butorphanol tartrate nasal spray was administered 30 minutes after the sumatriptan nasal spray, the AUC of butorphanol increased 11% and Cmax decreased 18%.

In neither case were the pharmacokinetics of sumatriptan affected by coadministration with butorphanol tartrate nasal spray. These results suggest that the analgesic effect of butorphanol tartrate nasal spray may be diminished when it is administered shortly after sumatriptan nasal spray, but by 30 minutes any such reduction in effect should be minimal.

The safety of using butorphanol tartrate nasal spray and IMITREX®1 (sumatriptan) nasal spray during the same episode of migrane has not been established. However, it should be noted that both products are capable of producing transient increases in blood pressure.

Cimetidine

The pharmacokinetics of a 1 mg dose of butorphanol administered as butorphanol tartrate nasal spray were not affected by the coadministration of cimetidine (300 mg QID). Conversely, the administration of butorphanol tartrate nasal spray (1 mg butorphanol QID) did not alter the pharmacokinetics of a 300 mg dose of cimetidine.

Oxymetazoline

The fraction of butorphanol tartrate nasal spray absorbed is unaffected by the concomitant administration of a nasal vasoconstrictor (oxymetazoline), but the rate of absorption is decreased. Therefore, a slower onset can be anticipated if butorphanol tartrate nasal spray is administered concomitantly with, or immediately following, a nasal vasoconstrictor.

Clinical Trials

The effectiveness of opioid analgesics varies in different pain syndromes.

Studies with butorphanol tartrate nasal spray have been performed in postoperative (general, orthopedic, oral, cesarean section) pain, in postepisiotomy pain, in pain of musculoskeletal origin, and in migraine headache pain (see below).

Use in the Management of Pain

Postoperative Pain: The analgesic efficacy of butorphanol tartrate nasal spray was evaluated (approximately 35 patients per treatment group) in a general and orthopedic surgery trial. Single doses of butorphanol tartrate nasal spray (1 or 2 mg) and IM meperidine (37.5 or 75 mg) were compared. Analgesia provided by 1 and 2 mg doses of butorphanol tartrate nasal spray was similar to 37.5 and 75 mg meperidine, respectively, with onset of analgesia within 15 minutes and peak analgesic effect within 1 hour. The median duration of pain relief was 2.5 hours with 1 mg butorphanol tartrate nasal spray, 3.5 hours with 2 mg butorphanol tartrate nasal spray and 3.3 hours with either dose of meperidine.

In a postcesarean section trial, butorphanol tartrate nasal spray administered to 35 patients as two 1 mg doses 60 minutes apart was compared with a single 2 mg dose of butorphanol tartrate nasal spray or a single 2 mg IV dose of butorphanol tartrate injection (37 patients each). Onset of analgesia was within 15 minutes for all butorphanol tartrate regimens. Peak analgesic effects of 2 mg intravenous butorphanol tartrate injection and butorphanol tartrate nasal spray were similar in magnitude. The duration of pain relief provided by both 2 mg butorphanol tartrate nasal spray regimens was approximately 4.5 hours and was greater than intravenous butorphanol tartrate injection (2.6 hours).

Migraine Headache Pain: The analgesic efficacy of two 1 mg doses 1 hour apart of butorphanol tartrate nasal spray in migraine headache pain was compared with a single dose of 10 mg IM methadone (31 and 32 patients, respectively). Significant onset of analgesia occurred within 15 minutes for both butorphanol tartrate nasal spray and IM methadone. Peak analgesic effect occurred at 2 hours for butorphanol tartrate nasal spray and 1.5 hours for methadone. The median duration of pain relief was 6 hours with butorphanol tartrate nasal spray and 4 hours with methadone as judged by the time when approximately half of the patients remedicated.

In two other trials in patients with migraine headache pain, a 2 mg initial dose of butorphanol tartrate nasal spray followed by an additional 1 mg dose 1 hour later (76 patients) was compared with either 75 mg IM meperidine (24 patients) or placebo (72 patients). Onset, peak activity and duration were similar with both active treatments; however, the incidence of adverse experiences (nausea, vomiting, dizziness) was higher in these two trials with the 2 mg initial dose of butorphanol tartrate nasal spray than in the trial with the 1 mg initial dose.

Individualization of Dosage

Use of butorphanol in geriatric patients, patients with renal impairment, patients with hepatic impairment, and during labor requires extra caution (see below and the appropriate sections in PRECAUTIONS).

The usual recommended dose for initial nasal administration is 1 mg (1 spray in one nostril). If adequate pain relief is not achieved within 60 to 90 minutes, an additional 1 mg dose may be given.

The initial dose sequence outlined above may be repeated in 3 to 4 hours as required after the second dose of the sequence.

For the management of severe pain, an initial dose of 2 mg (1 spray in each nostril) may be used in patients who will be able to remain recumbent in the event drowsiness or dizziness occurs. In such patients additional doses should not be given for 3 to 4 hours. The incidence of adverse events is higher with an initial 2 mg dose (see Clinical Trials).

The initial dose sequence in elderly patients and patients with renal or hepatic impairment should be limited to 1 mg followed, if needed, by 1 mg in 90 to 120 minutes. The repeat dose sequence in these patients should be determined by the patient’s response rather than at fixed times but will generally be no less than at 6-hour intervals (see PRECAUTIONS).

INDICATIONS AND USAGE

Butorphanol tartrate nasal spray is indicated for the management of pain severe enough to require an opioid analgesic and for which alternative treatments are inadequate.

Limitations of Use:

- Because of the risks of addiction, abuse, misuse, overdose, and death, which can occur at any dosage or duration, and persist over the course of therapy [see WARNINGS], reserve opioid analgesics, including butorphanol tartrate, for use in patients for whom alternative treatment options are ineffective, not tolerated, or would be otherwise inadequate to provide sufficient management of pain.

CONTRAINDICATIONS

Butorphanol tartrate nasal spray is contraindicated in:

- Patients with significant respiratory depression [see WARNINGS]
- Patients with acute or severe bronchial asthma in an unmonitored setting or in the absence of resuscitative equipment [see WARNINGS]
- Patients with known or suspected gastrointestinal obstruction, including paralytic ileus [see WARNINGS]
- Patients with hypersensitivity to butorphanol tartrate, the preservative benzethonium chloride, or any of the formulation excipients (e.g., anaphylaxis) [see WARNINGS])

WARNINGS

Addiction, Abuse, and Misuse

Butorphanol tartrate nasal spray contains butorphanol, a Schedule IV controlled substance. As an opioid, butorphanol tartrate nasal spray exposes users to the risks of addiction, abuse, and misuse [see DRUG ABUSE AND DEPENDENCE].

Although the risk of addiction in any individual is unknown, it can occur in patients appropriately prescribed butorphanol tartrate nasal spray. Addiction can occur at recommended dosages and if the drug is misused or abused. The risk of opioid-related overdose or overdose-related death is increased with higher opioid doses, and this risk persists over the course of therapy. In postmarketing studies, addiction, abuse, misuse, and fatal and non-fatal opioid overdose were observed in patients with long-term opioid use [see ADVERSE REACTIONS].

Assess each patient’s risk for opioid addiction, abuse, or misuse prior to prescribing butorphanol tartrate nasal spray, and reassess all patients receiving butorphanol tartrate nasal spray for the development of these behaviors and conditions. Risks are increased in patients with a personal or family history of substance abuse (including drug or alcohol abuse or addiction) or mental illness (e.g., major depression). The potential for these risks should not, however, prevent the proper management of pain in any given patient. Patients at increased risk may be prescribed opioids such as butorphanol tartrate nasal spray, but use in such patients necessitates intensive counseling about the risks and proper use of butorphanol tartrate nasal spray along with frequent reevaluation for signs of addiction, abuse, and misuse. Consider recommending or prescribing an opioid overdose reversal agent [WARNINGS, DOSAGE AND ADMINISTRATION].

Opioids are sought for nonmedical use and are subject to diversion from legitimate prescribed use. Consider these risks when prescribing or dispensing butorphanol tartrate nasal spray. Strategies to reduce these risks include prescribing the drug in the smallest appropriate quantity and advising the patient on careful storage of the drug during the course of treatment and proper disposal of unused drug. Contact local state professional licensing board or state-controlled substances authority for information on how to prevent and detect abuse or diversion of this product.

Life-Threatening Respiratory Depression

Serious, life-threatening, or fatal respiratory depression has been reported with the use of opioids, even when used as recommended. Respiratory depression, if not immediately recognized and treated, may lead to respiratory arrest and death. Management of respiratory depression may include close observation, supportive measures, and use of opioid overdose reversal agents (e.g., naloxone, nalmefene), depending on the patient’s clinical status [see OVERDOSAGE]. Carbon dioxide (CO2) retention from opioid-induced respiratory depression can exacerbate the sedating effects of opioids.

While serious, life-threatening, or fatal respiratory depression can occur at any time during the use of butorphanol tartrate nasal spray, the risk is greatest during the initiation of therapy or following a dosage increase.

To reduce the risk of respiratory depression, proper dosing and titration of butorphanol tartrate nasal spray are essential [see DOSAGE AND ADMINISTRATION]. Overestimating the butorphanol tartrate nasal spray dosage when converting patients from another opioid product can result in a fatal overdose with the first dose.

Accidental exposure to even one dose of butorphanol tartrate nasal spray, especially by children, can result in respiratory depression and death due to an overdose of butorphanol.

Educate patients and caregivers on how to recognize respiratory depression and emphasize the importance of calling 911 or getting emergency medical help right away in the event of a known or suspected overdose (see PRECAUTIONS, Information for Patients).

Opioids can cause sleep-related breathing disorders including central sleep apnea (CSA) and sleep-related hypoxemia. Opioid use increases the risk of CSA in a dose-dependent fashion. In patients who present with CSA, consider decreasing the opioid dosage using best practices for opioid taper [see DOSAGE AND ADMINISTRATION].

Patient Access to an Opioid Overdose Reversal Agent for the Emergency Treatment of Opioid Overdose

Inform patients and caregivers about opioid overdose reversal agents (e.g., naloxone, nalmefene). Discuss the importance of having access to an opioid overdose reversal agent, especially if the patient has risk factors for overdose (e.g., concomitant use of CNS depressants, a history of opioid use disorder, or prior opioid overdose) or if there are household members (including children) or other close contacts at risk for accidental ingestion or opioid overdose. The presence of risk factors for overdose should not prevent the management of pain in any patient [see WARNINGS]. Discuss the options for obtaining an opioid overdose reversal agent (e.g., prescription, over-the-counter, or as part of a community-based program).

There are important differences among the opioid overdose reversal agents, such as route of administration, product strength, approved patient age range, and pharmacokinetics. Be familiar with these differences, as outlined in the approved labeling for those products, prior to recommending or prescribing such an agent.

Educate patients and caregivers on how to recognize respiratory depression, and how to use an opioid overdose reversal agent for the emergency treatment of opioid overdose. Emphasize the importance of calling 911 or getting emergency medical help, even if an opioid overdose reversal agent is administered [see WARNINGS, OVERDOSAGE].

Risks from Concomitant Use with Benzodiazepines or Other CNS Depressants

Profound sedation, respiratory depression, coma, and death may result from the concomitant use of butorphanol tartrate nasal spray with benzodiazepines and/or other CNS depressants (e.g., alcohol, non-benzodiazepine, sedatives/hypnotics, anxiolytics, tranquilizers, muscle relaxants [i.e., cyclobenzaprine, metaxalone], general anesthetics, antipsychotics, gabapentinoids [gabapentin or pregabalin], and other opioids). Because of these risks, reserve concomitant prescribing of these drugs for use in patients for whom alternative treatment options are inadequate.

Observational studies have demonstrated that concomitant use of opioid analgesics and benzodiazepines increases the risk of drug-related mortality compared to use of opioid analgesics alone. Because of similar pharmacological properties, it is reasonable to expect similar risk with the concomitant use of other CNS depressant drugs with opioid analgesics [see PRECAUTIONS; Drug Interactions].

If the decision is made to prescribe a benzodiazepine or other CNS depressant concomitantly with an opioid analgesic, prescribe the lowest effective dosages and minimum durations of concomitant use. In patients already receiving an opioid analgesic, prescribe a lower initial dose of the benzodiazepine or other CNS depressant than indicated in the absence of an opioid, and titrate based on clinical response. If an opioid analgesic is initiated in a patient already taking a benzodiazepine or other CNS depressant, prescribe a lower initial dose of the opioid analgesic, and titrate based on clinical response. Inform patients and caregivers of this potential interaction, educate them on the signs and symptoms of respiratory depression (including sedation).

If concomitant use is warranted, consider recommending or prescribing an opioid overdose reversal agent [see WARNINGS, DOSAGE AND ADMINISTRATION, and OVERDOSAGE].

Advise both patients and caregivers about the risks of respiratory depression and sedation when levorphanol tartrate tablets are used with benzodiazepines or other CNS depressants (including alcohol and illicit drugs). Advise patients not to drive or operate heavy machinery until the effects of concomitant use of the benzodiazepine or other CNS depressant have been determined. Screen patients for risk of substance use disorders, including opioid abuse and misuse, and warn them of the risk for overdose and death associated with the use of additional CNS depressants including alcohol and illicit drugs [see PRECAUTIONS; Information for Patients/Caregivers, Drug Interactions].

Neonatal Opioid Withdrawal Syndrome

Use of butorphanol tartrate nasal spray for an extended period of time during pregnancy can result in withdrawal in the neonate. Neonatal opioid withdrawal syndrome, unlike opioid withdrawal syndrome in adults, may be life-threatening if not recognized and treated, and requires management according to protocols developed by neonatology experts. Observe newborns for signs of neonatal opioid withdrawal syndrome and manage accordingly. Advise pregnant women using opioids for an extended period of time of the risk of neonatal opioid withdrawal syndrome and ensure that appropriate treatment will be available [see PRECAUTIONS; Information for Patients, Pregnancy].

Opioid Analgesic Risk Evaluation and Mitigation Strategy (REMS)

To ensure that the benefits of opioid analgesics outweigh the risks of addiction, abuse, and misuse, the Food and Drug Administration (FDA) has required a Risk Evaluation and Mitigation Strategy (REMS) for these products. Under the requirements of the REMS, drug companies with approved opioid analgesic products must make REMS-compliant education programs available to healthcare providers. Healthcare providers are strongly encouraged to do all of the following:

- Complete a REMS-compliant education program offered by an accredited provider of continuing education (CE) or another education program that includes all the elements of the FDA Education Blueprint for Health Care Providers Involved in the Management or Support of Patients with Pain.
- Discuss the safe use, serious risks, and proper storage and disposal of opioid analgesics with patients and/or their caregivers every time these medicines are prescribed. The Patient Counseling Guide (PCG) can be obtained at this link: www.fda.gov/OpioidAnalgesicREMSPCG.
- Emphasize to patients and their caregivers the importance of reading the Medication Guide that they will receive from their pharmacist every time an opioid analgesic is dispensed to them.
- Consider. using other tools to improve patient, household, and community safety, such as patient-prescriber agreements that reinforce patient-prescriber responsibilities.

To obtain further information on the opioid analgesic REMS and for a list of accredited REMS CME/CE, call 800-503-0784, or log on to www.opioidanalgesicrems.com. The FDA Blueprint can be found at www.fda.gov/OpioidAnalgesicREMSBlueprint.

Risks of Concomitant Use or Discontinuation of Cytochrome P450 3A4 Inhibitors and Inducers

Concomitant use of butorphanol tartrate nasal spray with a CYP3A4 inhibitor, such as macrolide antibiotics (e.g., erythromycin), azole-antifungal agents (e.g., ketoconazole), and protease inhibitors (e.g., ritonavir), may increase plasma concentrations of butorphanol and prolong opioid adverse reactions, which may cause potentially fatal respiratory depression [see WARNINGS; Life-Threatening Respiratory Depression], particularly when an inhibitor is added after a stable dose of butorphanol tartrate nasal spray is achieved. Similarly, discontinuation of a CYP3A4 inducer, such as rifampin, carbamazepine, and phenytoin, in butorphanol tartrate nasal spray-treated patients may increase butorphanol plasma concentrations and prolong opioid adverse reactions. When using butorphanol tartrate nasal spray with CYP3A4 inhibitors or discontinuing CYP3A4 inducers in butorphanol tartrate nasal spray-treated patients, evaluate patients at frequent intervals and consider dosage reduction of butorphanol tartrate nasal spray until stable drug effects are achieved [see PRECAUTIONS; Drug Interactions].

Concomitant use of butorphanol tartrate nasal spray with CYP3A4 inducers or discontinuation of an CYP3A4 inhibitor could decrease butorphanol plasma concentrations, decrease opioid efficacy or, possibly, lead to a withdrawal syndrome in a patient who had developed physical dependence to butorphanol. When using butorphanol tartrate nasal spray with CYP3A4 inducers or discontinuing CYP3A4 inhibitors, monitor patients closely at frequent intervals and consider increasing the opioid dosage if needed to maintain adequate analgesia or if symptoms of opioid withdrawal occur [see PRECAUTIONS; Drug Interactions].

Opioid-Induced Hyperalgesia and Allodynia

Opioid-Induced Hyperalgesia (OIH) occurs when an opioid analgesic paradoxically causes an increase in pain, or an increase in sensitivity to pain. This condition differs from tolerance, which is the need for increasing doses of opioids to maintain a defined effect [see Dependence]. Symptoms of OIH include (but may not be limited to) increased levels of pain upon opioid dosage increase, decreased levels of pain upon opioid dosage decrease, or pain from ordinarily non-painful stimuli (allodynia). These symptoms may suggest OIH only if there is no evidence of underlying disease progression, opioid tolerance, opioid withdrawal, or addictive behavior.

Cases of OIH have been reported, both with short-term and longer-term use of opioid analgesics. Though the mechanism of OIH is not fully understood, multiple biochemical pathways have been implicated. Medical literature suggests a strong biologic plausibility between opioid analgesics and OIH and allodynia. If a patient is suspected to be experiencing OIH, carefully consider appropriately decreasing the dose of the current opioid analgesic or opioid rotation (safely switching the patient to a different opioid moiety) [see DOSAGE AND ADMINISTRATION; WARNINGS].

Life-Threatening Respiratory Depression in Patients with Chronic Pulmonary Disease or in Elderly, Cachectic, or Debilitated Patients

The use of butorphanol tartrate nasal spray in patients with acute or severe bronchial asthma in an unmonitored setting or in the absence of resuscitative equipment is contraindicated.

Patients with Chronic Pulmonary Disease

Butorphanol tartrate nasal spray -treated patients with significant chronic obstructive pulmonary disease or cor pulmonale, and those with a substantially decreased respiratory reserve, hypoxia, hypercapnia, or pre-existing respiratory depression are at increased risk of decreased respiratory drive including apnea, even at recommended dosages of butorphanol tartrate nasal spray [see WARNINGS].

Elderly, Cachetic, or Debilitated Patients

Life-threatening respiratory depression is more likely to occur in elderly, cachectic, or debilitated patients because they may have altered pharmacokinetics or altered clearance compared to younger, healthier patients [see WARNINGS].

Regularly evaluate patients, particularly when initiating and titrating butorphanol tartrate nasal spray and when butorphanol tartrate nasal spray is given concomitantly with other drugs that depress respiration [see WARNINGS]. Alternatively, consider the use of non-opioid analgesics in these patients.

Adrenal Insufficiency

Cases of adrenal insufficiency have been reported with opioid use, more often following greater than 1 month of use. Presentation of adrenal insufficiency may include non-specific symptoms and signs including nausea, vomiting, anorexia, fatigue, weakness, dizziness, and low blood pressure. If adrenal insufficiency is suspected, confirm the diagnosis with diagnostic testing as soon as possible. If adrenal insufficiency is diagnosed, treat with physiologic replacement doses of corticosteroids. Wean the patient off of the opioid to allow adrenal function to recover and continue corticosteroid treatment until adrenal function recovers. Other opioids may be tried as some cases reported use of a different opioid without recurrence of adrenal insufficiency. The information available does not identify any particular opioids as being more likely to be associated with adrenal insufficiency.

Risks of Use in Patients with Increased Intracranial Pressure, Brain Tumors, Head Injury, or Impaired Consciousness

In patients who may be susceptible to the intracranial effects of CO2 retention (e.g., those with evidence of increased intracranial pressure or brain tumors), butorphanol tartrate nasal spray may reduce respiratory drive, and the resultant CO2 retention can further increase intracranial pressure. Monitor such patients for signs of sedation and respiratory depression, particularly when initiating therapy with butorphanol tartrate nasal spray.

Opioids may also obscure the clinical course in a patient with a head injury. Avoid the use of butorphanol tartrate nasal spray in patients with impaired consciousness or coma.

Risks of Gastrointestinal Complications

Butorphanol tartrate nasal spray is contraindicated in patients with gastrointestinal obstruction, including paralytic ileus.

The butorphanol in butorphanol tartrate nasal spray may cause spasm of the sphincter of Oddi. Opioids may cause increases in serum amylase. Regularly evaluate patients with biliary tract disease, including acute pancreatitis, for worsening symptoms.

Cases of opioid-induced esophageal dysfunction (OIED) have been reported in patients taking opioids. The risk of OIED may increase as the dose and/or duration of opioids increases. Regularly evaluate patients for signs and symptoms of OIED (e.g., dysphagia, regurgitation, non-cardiac chest pain) and, if necessary, adjust opioid therapy as clinically appropriate [see CLINICAL PHARMACOLOGY].

Increased Risk of Seizures in Patients with Seizure Disorders

The butorphanol in butorphanol tartrate nasal spray may increase the frequency of seizures in patients with seizure disorders and may increase the risk of seizures occuring in other clinical settings associated with seizures. Regularly evaluate patients with a history of seizure disorders for worsened seizure control during butorphanol tartrate nasal spray therapy.

Withdrawal

Do not rapidly reduce or abruptly discontinue butorphanol tartrate nasal spray in a patient physically dependent on opioids. When discontinuing butorphanol tartrate nasal spray in a physically dependent patient, gradually taper the dosage. Rapid tapering of butorphanol tartrate nasal spray in a patient physically dependent on opioids may lead to a withdrawal syndrome and return of pain [see Dosage and Administration, Drug Abuse and Dependence].

Additionally, the use of butorphanol tartrate nasal spray, a mixed agonist/antagonist opioid analgesic, in patients who are receiving a full opioid agonist analgesic may reduce the analgesic effect and/or precipitate withdrawal symptoms. Avoid concomitant use of butorphanol tartrate nasal spray with a full opioid agonist analgesic.

Cardiovascular Effects

Because butorphanol may increase the work of the heart, especially the pulmonary circuit, the use of butorphanol tartrate nasal spray in patients with acute myocardial infarction, ventricular dysfunction, or coronary insufficiency should be limited to those situations where the benefits clearly outweigh the risk [see CLINICAL PHARMACOLOGY].

Severe hypertension has been reported rarely during butorphanol tartrate nasal spray therapy. In such cases, butorphanol tartrate nasal spray should be discontinued, and the hypertension treated with antihypertensive drugs. In patients who are not opioid dependent, naloxone has also been reported to be effective.

PRECAUTIONS

General

Hypotension associated with syncope during the first hour of dosing with butorphanol tartrate nasal spray has been reported rarely, particularly in patients with past history of similar reactions to opioid analgesics. Therefore, patients should be advised to avoid activities with potential risks.

Risks of Driving and Operating Machinery

Butorphanol tartrate nasal spray may impair the mental or physical abilities needed to perform potentially hazardous activities such as driving a car or operating machinery. Warn patients not to drive or operate dangerous machinery unless they are tolerant to the effects of butorphanol tartrate nasal spray and know how they will react to the medication [see PRECAUTIONS; Information for Patients].

Disorders of Respiratory Function or Control

Butorphanol may produce respiratory depression, especially in patients receiving other CNS active agents, or patients suffering from CNS diseases or respiratory impairment.

Hepatic and Renal Disease

In patients with hepatic or renal impairment, the initial dose sequence of butorphanol tartrate nasal spray should be limited to 1 mg followed, if needed, by 1 mg in 90 to 120 minutes. The repeat dose sequence in these patients should be determined by the patient's response rather than at fixed times but will generally be at intervals of no less than at 6 hours [see CLINICAL PHARMACOLOGY: Pharmacokinetics and Individualization of Dosage].

Information For Patients/Caregivers

Advise the patient to read the FDA-approved patient labeling (Medication Guide).

Storage and Disposal

Because of the risks associated with accidental ingestion, misuse, and abuse, advise patients to store butorphanol tartrate nasal spray securely, out of sight and reach of children, and in a location not accessible by others, including visitors to the home. Inform patients that leaving butorphanol tartrate nasal spray unsecured can pose a deadly risk to others in the home [see WARNINGS, DRUG ABUSE AND DEPENDENCE].

Addiction, Abuse, and Misuse
Inform patients that the use of butorphanol tartrate nasal spray, even when taken as recommended, can result in addiction, abuse, and misuse, which can lead to overdose and death [see WARNINGS]. Instruct patients not to share butorphanol tartrate nasal spray with others and to take steps to protect butorphanol tartrate nasal spray from theft or misuse.

Life-Threatening Respiratory Depression
Inform patients of the risk of life-threatening respiratory depression, including information that the risk is greatest when starting butorphanol tartrate nasal spray or when the dosage is increased, and that it can occur even at recommended dosages.

Educate patients and caregivers on how to recognize respiratory depression and emphasize the importance of calling 911 or getting emergency medical help right away in the event of a known or suspected overdose (see WARNINGS, Life Threatening Respiratory Depression).

Accidental Exposure

Inform patients that accidental exposure, especially by children, may result in respiratory depression or death [see WARNINGS]. Instruct patients to take steps to store butorphanol tartrate nasal spray securely and to dispose of unused butorphanol tartrate nasal spray by unscrewing the cap, rinsing the bottle, and placing the parts in the waste container.

Interactions with Benzodiazepines and Other CNS Depressants

Inform patients and caregivers that potentially fatal additive effects may occur if butorphanol tartrate nasal spray is used with benzodiazepines or other CNS depressants, including alcohol (e.g., non-benzodiazepine sedative/hypnotics, anxiolytics, tranquilizers, muscle relaxants, general anesthetics, antipsychotics, gabapentinoids [gabapentin or pregabalin], and other opioids), and not to use these concomitantly unless supervised by a healthcare provider [see WARNINGS, PRECAUTIONS; Drug Interactions].

Patient Access to an Opioid Overdose Reversal Agent for the Emergency Treatment of Opioid Overdose

Inform patients and caregivers about opioid overdose reversal agents (e.g., naloxone, nalmefene). Discuss the importance of having access to an opioid overdose reversal agent, especially if the patient has risk factors for overdose (e.g., concomitant use of CNS depressants, a history of opioid use disorder, or prior opioid overdose) or if there are household members (including children) or other close contacts at risk for accidental ingestion or opioid overdose.

Discuss with the patient the options for obtaining an opioid overdose reversal agent (e.g., prescription, over-the-counter, or as part of a community-based program) [see WARNINGS, DOSAGE AND ADMINISTRATION].

Educate patients and caregivers on how to recognize the signs and symptoms of an overdose.

Explain to patients and caregivers that effects of opioid overdose reversal agents like naloxone and nalmefene are temporary, and that they must call 911 or get emergency medical help right away in all cases of known or suspected opioid overdose, even if an opioid overdose reversal agent is administered [see OVERDOSAGE].

Advise patients and caregivers:

- how to treat with the overdose reversal agent in the event of an opioid overdose.
- to tell family and friends about the opioid overdose reversal agent, and to keep it in a place where family and friends can access it in an emergency.
- to read the Patient Information (or other educational material) that will come with their opioid overdose reversal agent. Emphasize the importance of doing this before an opioid emergency happens, so the patient and caregiver will know what to do.

Hyperalgesia and Allodynia

Inform patients and caregivers not to increase opioid dosage without first consulting a clinician. Advise patients to seek medical attention if they experience symptoms of hyperalgesia, including worsening pain, increased sensitivity to pain, or new pain [see WARNINGS, ADVERSE REACTIONS].

Serotonin Syndrome
Inform patients that opioids could cause a rare but potentially life-threatening condition resulting from concomitant administration of serotonergic drugs. Warn patients of the symptoms of serotonin syndrome and to seek medical attention right away if symptoms develop. Instruct patients to inform their healthcare providers if they are taking, or plan to take serotonergic medications [see PRECAUTIONS; Drug Interactions].

Important Administration Instructions

Inform patients of the proper use of butorphanol tartrate nasal spray [see PATIENT INSTRUCTIONS and MEDICATION GUIDE].

Important Discontinuation Instructions

In order to avoid developing withdrawal symptoms, instruct patients not to discontinue butorphanol tartrate nasal spray without first discussing a tapering plan with the prescriber [see DOSAGE AND ADMINISTRATION]

Driving or Operating Heavy Machinery

Inform patients that butorphanol tartrate nasal spray may impair the mental and/or physical abilities required for the performance of potentially hazardous tasks such as driving a car or operating machinery and to avoid such tasks while taking this product, until they know how they will react to the medication [see WARNINGS].

Constipation

Advise patients of the potential for severe constipation, including management instructions and when to seek medical attention [see ADVERSE REACTIONS, CLINICAL PHARMACOLOGY].

Adrenal Insufficiency

Inform patients that opioids could cause adrenal insufficiency, a potentially life-threatening condition. Adrenal insufficiency may present with non-specific symptoms and signs such as nausea, vomiting, anorexia, fatigue, weakness, dizziness, and low blood pressure. Advise patients to seek medical attention if they experience a constellation of these symptoms [see WARNINGS].

Anaphylaxis
Inform patients that anaphylaxis has been reported with ingredients contained in butorphanol tartrate nasal spray. Advise patients how to recognize such a reaction and when to seek medical attention [see CONTRAINDICATIONS, ADVERSE REACTIONS].

Pregnancy
Neonatal Opioid Withdrawal Syndrome
Inform female patients of reproductive potential that use of butorphanol tartrate nasal spray for an extended period of time during pregnancy can result in neonatal opioid withdrawal syndrome, which may be life-threatening if not recognized and treated [see WARNINGS, PRECAUTIONS; Pregnancy].

Embryo-Fetal Toxicity
Inform female patients of reproductive potential that butorphanol tartrate nasal spray can cause fetal harm and to inform the healthcare provider of a known or suspected pregnancy [see PRECAUTIONS; Pregnancy].

Lactation
Advise nursing mothers to carefully observe infants for increased sleepiness (more than usual), breathing difficulties, or limpness. Instruct nursing mothers to seek immediate medical care if they notice these signs [see PRECAUTIONS; Nursing Mothers].

Infertility
Inform patients that use of opioids for an extended period of time may cause reduced fertility. It is not known whether these effects on fertility are reversible [see ADVERSE REACTIONS].

Disposal of Unused Butorphanol Tartrate
Advise patients to dispose of butorphanol tartrate by unscrewing the cap, rinsing the bottle, and placing the parts in a waste container.

Drug Interactions

Benzodiazepine and Other Central Nervous System (CNS) Depressants

Due to additive pharmacologic effect, the concomitant use of benzodiazepines or other CNS depressants, such as alcohol, other sedative hypnotics, anxiolytics, and tranquilizers, muscle relaxants (i.e., cyclobenzaprine, metaxalone), general anesthetics, antipsychotics, gabapentinoids (gabapentin or pregabalin), and other opioids, can increase the risk of hypotension, respiratory depression, profound sedation, coma, and death.

Reserve concomitant prescribing of these drugs for use in patients for whom alternative treatment options are inadequate. Limit dosages and durations to the minimum required. Inform patients and caregivers of this potential interaction and educate them on the signs and symptoms of respiratory depression (including sedation). If concomitant use is warranted, consider recommending or prescribing an opioid overdose reversal agent [see WARNINGS, DOSAGE AND ADMINISTRATION].

Serotonergic Drugs

The concomitant use of opioids with other drugs that affect the serotonergic neurotransmitter system, such as selective serotonin reuptake inhibitors (SSRIs), serotonin and norepinephrine reuptake inhibitors (SNRIs), tricyclic antidepressants (TCAs), triptans, 5-HT3 receptor antagonists, drugs that affect the serotonin neurotransmitter system (e.g., mirtazapine, trazodone, tramadol), certain muscle relaxants (i.e., cyclobenzaprine, metaxalone), monoamine oxidase (MAO) inhibitors (those intended to treat psychiatric disorders and also others, such as linezolid and intravenous methylene blue), has resulted in serotonin syndrome [see PRECAUTIONS; Information for Patients].

If concomitant use is warranted, frequently evaluate the patient, particularly during treatment initiation and dose adjustment. Discontinue butorphanol tartrate nasal spray immediately if serotonin syndrome is suspected.

Cytochrome P450 (CYP 450) Interactions

It is not known if the effects of butorphanol tartrate nasal spray are altered by concomitant medications that affect hepatic metabolism of drugs (CYP 450 inhibitors or inducers) (e.g., erythromycin, theophylline, etc.), but physicians should be alert to the possibility that a smaller initial dose and longer intervals between doses may be needed.

Monoamine Oxidase inhibitors (MAOIs)

No information is available about the use of butorphanol concurrently with MAO inhibitors.

Advise patient to avoid concomitant use of these drugs.

Carcinogenesis, Mutagenesis, Impairment of Fertility

Carcinogenesis

Two-year carcinogenicity studies were conducted in mice and rats given butorphanol tartrate in the diet up to 60 mg/kg/day (24 and 48 times the human daily dose of 12 mg/day based on a body surface area comparison, respectively). There was no evidence of carcinogenicity in either species in these studies.

Mutagenesis

Butorphanol was not genotoxic in the in vitro bacterial reverse mutation assay (Ames) or in an in vitro unscheduled DNA synthesis and repair assay conducted in cultured human fibroblast cells.

Impairment of fertility

In a study where male rats were treated subcutaneously with 0.5 or 2.5 mg/kg butorphanol for 75 days prior to mating to female rats treated subcutaneously with 0.5 or 2.5 mg/kg butorphanol for 14-days prior to mating and throughout gestation and lactation, no adverse effects on fertility were noted (0.4- and 2-times the human daily dose of 12 mg based on body surface area).

In a study where male rats were treated orally with 10, 40, or 160 mg/kg for 63 days prior to mating to female rats treated orally with the same doses of butorphanol for 14 days prior to mating, reduced pregnancy rates were reported in the high dose group (130-times the human daily dose of 12 mg based on body surface area).

Pregnancy

Reproduction studies in mice, rats, and rabbits during organogenesis did not reveal any teratogenic potential to butorphanol. However, pregnant rats treated subcutaneously with butorphanol at 1 mg/kg (5.9 mg/m^2) had a higher frequency of stillbirths than controls. Butorphanol at 30 mg/kg/oral (360 mg/m^2) and 60 mg/kg/oral (720 mg/m^2) also showed higher incidences of post-implantation loss in rabbits.

There are no adequate and well-controlled studies of butorphanol tartrate nasal spray in pregnant women before 37 weeks of gestation. Butorphanol tartrate nasal spray should be used during pregnancy only if the potential benefit justifies the potential risk to the infant.

Fetal/Neonatal Adverse Reactions

Use of opioid analgesics for an extended period of time during pregnancy for medical or nonmedical purposes can result in physical dependence in the neonate and neonatal opioid withdrawal syndrome shortly after birth.

Neonatal opioid withdrawal syndrome presents as irritability, hyperactivity and abnormal sleep pattern, high pitched cry, tremor, vomiting, diarrhea, and failure to gain weight. The onset, duration, and severity of neonatal opioid withdrawal syndrome vary based on the specific opioid used, duration of use, timing and amount of last maternal use, and rate of elimination of the drug by the newborn. Observe newborns for symptoms of neonatal opioid withdrawal syndrome and manage accordingly [see WARNINGS].

Labor or Delivery

Opioids cross the placenta and may produce respiratory depression and psycho-physiologic effects in neonates. An opioid overdose reversal agent, such as naloxone or nalmefene, must be available for reversal of opioid-induced respiratory depression in the neonate. Butorphanol tartrate nasal spray is not recommended for use in pregnant women during or immediately prior to labor, when other analgesic techniques are more appropriate. Opioid analgesics, including butorphanol tartrate nasal spray, can prolong labor through actions which temporarily reduce the strength, duration, and frequency of uterine contractions. However, this effect is not consistent and may be offset by an increased rate of cervical dilation, which tends to shorten labor. Monitor neonates exposed to opioid analgesics during labor for signs of excess sedation and respiratory depression.

Butorphanol tartrate nasal spray is not recommended during labor or delivery because there is no clinical experience with its use in this setting.

Nursing Mothers

Although there is no clinical experience with the use of butorphanol tartrate nasal spray in nursing mothers, butorphanol has been detected in milk following administration of butorphanol tartrate injection to nursing mothers. The amount an infant would receive is probably clinically insignificant (estimated 4 mcg/L of milk in a mother receiving 2 mg IM four times a day). It should be assumed that butorphanol will appear in the milk in similar amounts following the nasal route of administration.

The developmental and health benefits of breastfeeding should be considered along with the mother’s clinical need for butorphanol tartrate nasal spray and any potential adverse effects on the breastfed infant from butorphanol or from the underlying maternal condition.

Infants exposed to butorphanol tartrate nasal spray through breast milk should be monitored for excess sedation and respiratory depression. Withdrawal symptoms can occur in breastfed infants when maternal administration of an opioid analgesic is stopped, or when breast-feeding is stopped.

Females and Males of Reproductive Potential

Infertility

Use of opioids for an extended period of time may cause reduced fertility in females and males of reproductive potential. It is not known whether these effects on fertility are reversible (see CLINICAL PHARMACOLOGY, PRECAUTIONS, Carcinogenesis, Mutagenesis, Impairment of Fertility and ADVERSE REACTIONS).

Pediatric Use

Butorphanol tartrate nasal spray is not recommended for use in patients below 18 years of age because safety and efficacy have not been established in this population.

Geriatric Use

Elderly patients (aged 65 years or older) may have increased sensitivity to butorphanol tartrate nasal spray.

Of the approximately 1700 patients treated with butorphanol tartrate nasal spray in clinical studies, 8% were 65 years of age or older and 2% were 75 years or older.

Due to changes in clearance, the mean half-life of butorphanol is increased by 25% (to over 6 hours) in patients over the age of 65 years [see CLINICAL PHARMACOLOGY: Pharmacokinetics]. Elderly patients may be more sensitive to the side effects of butorphanol. In clinical studies of butorphanol tartrate nasal spray, elderly patients had an increased frequency of headache, dizziness, drowsiness, vertigo, constipation, nausea and/or vomiting, and nasal congestion compared with younger patients. There are insufficient efficacy data for patients ≥65 years to determine whether they respond differently from younger patients.

Initially a 1 mg dose of butorphanol tartrate nasal spray should be generally used in geriatric patients and 90 to 120 minutes should elapse before administering a second 1 mg dose, if needed [see CLINICAL PHARMACOLOGY: Individualization of Dosage].

In general, use caution when selecting a dosage for an elderly patient, usually starting at the low end of the dosing range, reflecting the greater frequency of decreased hepatic, renal, or cardiac function and of concomitant disease or other drug therapy [see DOSAGE AND ADMINISTRATION].

Respiratory depression is the chief risk for elderly patients treated with opioids and has occurred after large initial doses were administered to patients who were not opioid-tolerant or when opioids were co-administered with other agents that depress respiration. Titrate the dosage of butorphanol tartrate nasal spray slowly in geriatric patients and frequently reevaluate the patient for signs of central nervous system and respiratory depression [see WARNINGS].

This drug is known to be substantially excreted by the kidney, and the risk of adverse reactions to this drug may be greater in patients with impaired renal function. Because elderly patients are more likely to have decreased renal function, care should be taken in dose selection, and it may be useful to regularly evaluate renal function.

ADVERSE REACTIONS

Clinical Trial Experience

A total of 788 patients were studied in premarketing clinical trials of butorphanol tartrate nasal spray. In nearly all cases the type and incidence of side effects with butorphanol were those commonly observed with opioid analgesics.

The adverse experiences described below are based on data from short-term and long-term clinical trials in patients receiving intranasal butorphanol, except acute studies in normal subjects. There has been no attempt to correct for placebo effect or to subtract the frequencies reported by placebo-treated patients in controlled trials.

The most frequently reported adverse experiences across all clinical trials with Butorphanol Tartrate Nasal Spray were somnolence (49%), dizziness (23%), nausea and/or vomiting (8%). In long-term trials with butorphanol tartrate nasal spray only, nasal congestion (13%) and insomnia (11%) were frequently reported.

The following adverse experiences were reported at a frequency of 1% or greater in clinical trials and were considered to be probably related to the use of butorphanol.

Body as a Whole: Asthenia/lethargy, headache, sensation of heat, pain.

Cardiovascular: Hypertension, hypotension

Digestive: Anorexia, constipation, dry mouth, nausea and/or vomiting, diarrhea.

Nervous: Anxiety, confusion, dizziness, euphoria, floating feeling, insomnia, nervousness, paresthesia, somnolence, tremor

Respiratory: Epistaxis, nasal congestion, nasal irritation, rhinitis, sinus congestion, sinusitis, nose pain.

Skin and Appendages: Sweating, pruritus

Special Senses: Blurred vision, ear pain, tinnitus, unpleasant taste

The following adverse experiences were reported with a frequency of less than 1% in clinical trials and were considered to be probably related to the use of butorphanol.

Cardiovascular: Hypotension, syncope

Nervous: Abnormal dreams, agitation, dysphoria, hallucinations, hostility, withdrawal symptoms

Skin and Appendages: Rash/hives

Urogenital: Impaired urination

The following infrequent additional adverse experiences were reported in a frequency of less than 1% of the patients studied in short-term butorphanol tartrate nasal spray trials or trials of butorphanol tartrate injection and under circumstances where the association between these events and butorphanol administration is unknown. They are being listed as alerting information for the physician due to their clinical significance.

Body as a Whole: edema.

Cardiovascular: chest pain, hypertension, tachycardia.

Nervous: depression.

Respiratory: shallow breathing.

Hypoglycemia: Cases of hypoglycemia have been reported in patients taking opioids. Most reports were in patients with at least one predisposing risk factor (e.g., diabetes).

Postmarketing Experience

The following adverse reactions have been identified during post approval use of butorphanol tartrate nasal spray. Because these reactions are reported voluntarily from a population of uncertain size, it is not always possible to reliably estimate their frequency or establish a causal relationship to drug exposure.

- Serotonin syndrome: Cases of serotonin syndrome, a potentially life-threatening condition, have been reported during concomitant use of opioids with serotonergic drugs.
- Adrenal insufficiency: Cases of adrenal insufficiency have been reported with opioid use, more often following greater than one month of use.
- Anaphylaxis: Anaphylaxis has been reported with ingredients contained in butorphanol tartrate nasal spray.
- Androgen deficiency: Cases of androgen deficiency have occurred with use of opioids for an extended period of time. [see CLINICAL PHARMACOLOGY].
- Hyperalgesia and Allodynia: Cases of hyperalgesia and allodynia have been reported with opioid therapy of any duration [see WARNINGS].
- Opioid-induced esophageal dysfunction (OIED): Cases of OIED have been reported in patients taking opioids and may occur more frequently in patients taking higher doses of opioids, and/or in patients taking opioids longer term [see WARNINGS].

Adverse Reactions from Observational Studies

A prospective, observational cohort study estimated the risks of addiction, abuse, and misuse in patients initiating long-term use of Schedule II opioid analgesics between 2017 and 2021. Study participants included in one or more analyses had been enrolled in selected insurance plans or health systems for at least one year, were free of at least one outcome at baseline, completed a minimum number of follow-up assessments, and either: 1) filled multiple extended-release/long-acting opioid analgesic prescriptions during a 90-day period (n=978); or 2) filled any Schedule II opioid analgesic prescriptions covering at least 70 of 90 days (n=1,244). Those included also had no dispensing of the qualifying opioids in the previous 6 months.

Over 12 months:

- approximately 1% to 6% of participants across the two cohorts newly met criteria for addiction, as assessed with two validated interview based measures of moderate-to-severe opioid use disorder based on Diagnostic and Statistical Manual of Mental Disorders, Fifth Edition (DSM-5) criteria, and
- approximately 9% and 22% of participants across the two cohorts newly met criteria for prescription opioid abuse and misuse [defined in DRUG ABUSE AND DEPENDENCE], respectively, as measured with a validated self-reported instrument.

A retrospective, observational cohort study estimated the risk of opioid involved overdose or opioid overdose-related death in patients with new long-term use of Schedule II opioid analgesics from 2006 through 2016 (n=2,20,249). Included patients had been enrolled in either one of two commercial insurance programs, one managed care program, or one Medicaid program for at least 9 months. New long-term use was defined as having Schedule II opioid analgesic prescriptions covering at least 70 days’ supply over the 3 months prior to study entry and none during the preceding 6 months. Patients were excluded if they had an opioid-involved overdose in the 9 months prior to study entry. Overdose was measured using a validated medical code-based algorithm with linkage to the National Death Index database. The 5-year cumulative incidence estimates for opioid-involved overdose or opioid overdose-related death ranged from approximately 1.5% to 4% across study sites, counting only the first event during follow-up. Approximately 17% of first opioid overdoses observed over the entire study period (5 to 11 years, depending on the study site) were fatal. Higher baseline opioid dose was the strongest and most consistent predictor of opioid-involved overdose or opioid overdose-related death. Study exclusion criteria may have selected patients at lower risk of overdose, and substantial loss to follow-up (approximately 80%) also may have biased estimates.

The risk estimates from the studies described above may not be generalizable to all patients receiving opioid analgesics, such as those with exposures shorter or longer than the duration evaluated in the studies.

DRUG ABUSE AND DEPENDENCE

Controlled Substance

Butorphanol tartrate nasal spray contains butorphanol, a Schedule IV controlled substance.

Abuse

Butorphanol tartrate nasal spray contains butorphanol tartrate, a substance with a high potential for misuse and abuse, which can lead to the development of substance use disorder, including addiction [see WARNINGS].

Misuse is the intentional use, for therapeutic purposes, of a drug by an individual in a way other than prescribed by a healthcare provider or for whom it was not prescribed.

Abuse is the intentional non-therapeutic use of a drug, even once, for its desirable psychological or physiological effects.

Drug addiction is a cluster of behavioral, cognitive, and physiological phenomena that may include a strong desire to take the drug, difficulties in controlling drug use (e.g., continuing drug use despite harmful consequences, giving a higher priority to drug use than other activities and obligations), and possible tolerance or physical dependence.

Misuse and abuse of butorphanol tartrate nasal spray increases risk of overdose, which may lead to central nervous system and respiratory depression, hypotension, seizures, and death. The risk is increased with concurrent abuse of butorphanol tartrate nasal spray with alcohol and other CNS depressants. Abuse of and addiction to opioids in some individuals may not be accompanied by concurrent tolerance and symptoms of physical dependence. In addition, abuse of opioids can occur in the absence of addiction.

All patients treated with opioids require careful and frequent reevaluation for signs of misuse, abuse, and addiction, because use of opioid analgesic products carries the risk of addiction even under appropriate medical use. Patients at high risk of butorphanol tartrate nasal spray abuse include those with a history of prolonged use of any opioid, including products containing butorphanol tartrate, those with a history of drug or alcohol abuse, or those who use butorphanol tartrate nasal spray in combination with other abused drugs.

“Drug-seeking” behavior is very common in persons with substance use disorders. Drug-seeking tactics include emergency calls or visits near the end of office hours, refusal to undergo appropriate examination, testing, or referral, repeated “loss” of prescriptions, tampering with prescriptions, and reluctance to provide prior medical records or contact information for other treating healthcare provider(s). “Doctor shopping” (visiting multiple prescribers to obtain additional prescriptions) is common among people who abuse drugs and people with substance use disorder Preoccupation with achieving adequate pain relief can be appropriate behavior in a patient with inadequate pain control.

Butorphanol tartrate nasal spray, like other opioids, can be diverted for nonmedical use into illicit channels of distribution. Careful record-keeping of prescribing information, including quantity, frequency, and renewal requests, as required by state and federal law, is strongly advised.

Proper assessment of the patient, proper prescribing practices, periodic reevaluation of therapy, and proper dispensing and storage are appropriate measures that help to limit abuse of opioid drugs.

Risks Specific to Abuse of Butorphanol Tartrate Nasal Spray

Abuse of butorphanol tartrate nasal spray poses a risk of overdose and death. The risk is increased with concurrent use of butorphanol tartrate nasal spray with alcohol and/or other CNS depressants.

Parenteral drug abuse is commonly associated with transmission of infectious diseases such as hepatitis and HIV.

Dependence

Both tolerance and physical dependence can develop during use of opioid therapy.

Tolerance is a physiological state characterized by a reduced response to a drug after repeated administration (i.e., a higher dose of a drug is required to produce the same effect that was once obtained at a lower dose).

Physical dependence is a state that develops as a result of a physiological adaptation in response to repeated drug use, manifested by withdrawal signs and symptoms after abrupt discontinuation or a significant dose reduction of a drug.

Withdrawal may be precipitated through the administration of drugs with opioid antagonist activity (e.g., naloxone, nalmefene), mixed agonist/antagonist analgesics (e.g., pentazocine, butorphanol, nalbuphine), or partial agonists (e.g., buprenorphine). Physical dependence may not occur to a clinically significant degree until after several days to weeks of continued use.

Do not rapidly reduce or abruptly discontinue butorphanol tartrate nasal spray in a patient physically dependent on opioids. Rapid tapering of butorphanol tartrate nasal spray in a patient physically dependent on opioids may lead to serious withdrawal symptoms, uncontrolled pain, and suicide. Rapid discontinuation has also been associated with attempts to find other sources of opioid analgesics, which may be confused with drug-seeking for abuse.

When discontinuing butorphanol tartrate nasal spray, gradually taper the dosage using a patient-specific plan that considers the following: the dose of butorphanol tartrate nasal spray the patient has been taking, the duration of treatment, and the physical and psychological attributes of the patient. To improve the likelihood of a successful taper and minimize withdrawal symptoms, it is important that the opioid tapering schedule is agreed upon by the patient. In patients taking opioids for an extended period of time at high doses, ensure that a multimodal approach to pain management, including mental health support (if needed), is in place prior to initiating an opioid analgesic taper [see DOSAGE AND ADMINISTRATION, and WARNINGS].

Infants born to mothers physically dependent on opioids will also be physically dependent and may exhibit respiratory difficulties and withdrawal signs [see Pregnancy].

OVERDOSAGE

Clinical Presentation

Acute overdose with butorphanol tartrate can be manifested by respiratory depression, somnolence progressing to stupor or coma, skeletal muscle flaccidity, cold and clammy skin, constricted pupils, and in some cases, pulmonary edema, bradycardia, hypotension, hypoglycemia, partial or complete airway obstruction, atypical snoring, and death. Marked mydriasis rather than miosis may be seen with hypoxia in overdose situations [see CLINICAL PHARMACOLOGY]. Toxic leukoencephalopathy has been reported after opioid overdose and can present hours, days, or weeks after apparent recovery from the initial intoxication.

Treatment of Overdose

In case of overdose, priorities are the reestablishment of a patent and protected airway and institution of assisted or controlled ventilation, if needed. Employ other supportive measures (including oxygen and vasopressors) in the management of circulatory shock and pulmonary edema as indicated. Cardiac arrest or arrhythmias will require advanced life-support measures.

For clinically significant respiratory or circulatory depression secondary to butorphanol tartrate overdose, administer an opioid overdose reversal agent such as naloxone or nalmefene. As butorphanol is a mixed opioid agonist/antagonist, larger doses of naloxone may be needed to reverse the effects of an overdose.

Because the duration of opioid reversal is expected to be less than the duration of action of butorphanol in butorphanol tartrate nasal spray, carefully monitor the patient until spontaneous respiration is reliably re-established. If the response to an opioid overdose reversal agent is suboptimal or only brief in nature, administer additional reversal agent as directed by the product’s prescribing information.

In an individual physically dependent on opioids, administration of the recommended usual dosage of the overdose reversal agent will precipitate an acute withdrawal syndrome. The severity of the withdrawal symptoms experienced will depend on the degree of physical dependence and the dose of the reversal agent administered. If a decision is made to treat serious respiratory depression in the physically dependent patient, administration of the reversal agent should be initiated with care and by titration with smaller than usual doses of the reversal agent.

DOSAGE AND ADMINISTRATION

Important Dosage and Administration Instructions

Butorphanol tartrate nasal spray should be prescribed only by healthcare professionals who are knowledgeable about the use of opioids and how to mitigate the associated risks.

Use the lowest effective dosage for the shortest duration of time consistent with individual patient treatment goals [see WARNINGS]. Because the risk of overdose increases as opioid doses increase, reserve titration to higher doses of butorphanol tartrate nasal spray for patients in whom lower doses are insufficiently effective and in whom the expected benefits of using a higher dose opioid clearly outweigh the substantial risks.

Many acute pain conditions (e.g., the pain that occurs with a number of surgical procedures or acute musculoskeletal injuries) require no more than a few days of an opioid analgesic. Clinical guidelines on opioid prescribing for some acute pain conditions are available.

There is variability in the opioid analgesic dose and duration needed to adequately manage pain due both to the cause of pain and to individual patient factors. Initiate the dosing regimen for each patient individually, taking into account the patient’s underlying cause and severity of pain, prior analgesic treatment and response, and risk factors for addiction, abuse, and misuse [see WARNINGS].

Respiratory depression can occur at any time during opioid therapy, especially when initiating and following dosage increases with butorphanol tartrate nasal spray. Consider this risk when selecting an initial dose and when making dose adjustments [see WARNINGS].

Patient Access to an Opioid Overdose Reversal Agent for the Emergency Treatment of Opioid Overdose

Inform patients and caregivers about opioid overdose reversal agents (e.g., naloxone, nalmefene). Discuss the importance of having access to an opioid overdose reversal agent, especially if the patient has risk factors for overdose (e.g., concomitant use of CNS depressants, a history of opioid use disorder, or prior opioid overdose) or if there are household members (including children) or other close contacts at risk for accidental ingestion or opioid overdose. The presence of risk factors for overdose should not prevent the management of pain in any patient [see WARNINGS; Addiction, Abuse, and Misuse; Life-Threatening Respiratory Depression; Risks from Concomitant Use with Benzodiazepines or Other CNS Depressants].

Discuss the options for obtaining an opioid overdose reversal agent (e.g., prescription, over-the-counter, or as part of a community-based program).

There are important differences among the opioid overdose reversal agents, such as route of administration, product strength, approved patient age range, and pharmacokinetics. Be familiar with these differences, as outlined in the approved labeling for those products, prior to recommending or prescribing such an agent.

Initial Dosage

Use of Butorphanol Tartrate Nasal Spray as the first Opioid Analgesic

Factors to be considered in determining the dose are age, body weight, physical status, underlying pathological condition, use of other drugs, type of anesthesia to be used, and surgical procedure involved. Use in the elderly and in patients with hepatic or renal disease requires extra caution (see PRECAUTIONS and CLINICAL PHARMACOLOGY: Individualization of Dosage). The following doses are for patients who do not have impaired hepatic or renal function and who are not on CNS active agents.

Use for Pain: Initiate treatment with butorphanol tartrate nasal spray in a dosing range of 1 mg (1 spray in one nostril) to 2 mg (1 spray in each nostril) every 3 to 4 hours as needed for pain, at the lowest dose necessary to achieve adequate analgesia. Titrate the dose based upon the individual patient’s response to their initial dose of butorphanol tartrate nasal spray. The usual recommended dose for initial nasal administration of butorphanol tartrate nasal spray is 1 mg (1 spray in one nostril). Adherence to this dose reduces the incidence of drowsiness and dizziness. If adequate pain relief is not achieved within 60 to 90 minutes, an additional 1 mg dose may be given.

The initial dose sequence outlined above may be repeated in 3 to 4 hours as required after the second dose of the sequence.

Depending on the severity of the pain, an initial dose of 2 mg (1 spray in each nostril) may be used in patients who will be able to remain recumbent in the event drowsiness or dizziness occurs. In such patients single additional 2 mg doses should not be given for 3 to 4 hours.

Use in Balanced Anesthesia: The use of butorphanol tartrate nasal spray is not recommended because it has not been studied in induction or maintenance of anesthesia.

Labor: The use of butorphanol tartrate nasal spray is not recommended as it has not been studied in labor.

Conversion from Other Opioids to Butorphanol Tartrate Nasal Spray

There is inter-patient variability in the potency of opioid drugs and opioid formulations. Therefore, a conservative approach is advised when determining the total daily dosage of butorphanol tartrate nasal spray. It is safer to underestimate a patient’s 24-hour butorphanol tartrate nasal spray dosage than to overestimate the 24-hour butorphanol dosage and manage an adverse reaction due to overdose

Dosage Modifications in Elderly Patients and Patients with Renal or Hepatic Impairment The initial dose sequence in elderly patients and patients with hepatic or renal impairment should be limited to 1 mg followed, if needed, by 1 mg in 90 to 120 minutes. The repeat dose sequence should be determined by the patient’s response rather than at fixed times but will generally be no less than at 6 hours intervals [see CLINICAL PHARMACOLOGY: Individualization of Dosage and PRECAUTIONS].

Titration and Maintenance of Therapy

Individually titrate butorphanol tartrate nasal spray to a dose that provides adequate analgesia and minimizes adverse reactions. Continually reevaluate patients receiving butorphanol tartrate nasal spray to assess the maintenance of pain control, signs and symptoms of opioid withdrawal, and other adverse reaction as well as reassessing for the development of addiction, abuse, or misuse [see WARNINGS]. Frequent communication is important among the prescriber, other members of the healthcare team, the patient, and the caregiver/family during periods of changing analgesic requirements, including initial titration.

If the level of pain increases after dosage stabilization, attempt to identify the source of increased pain before increasing the butorphanol tartrate nasal spray dosage. If after increasing the dosage, unacceptable opioid-related adverse reactions are observed (including an increase in pain after dosage increase), consider reducing the dosage [see WARNINGS]. Adjust the dosage to obtain an appropriate balance between management of pain and opioid-related adverse reactions.

Safe Reduction or Discontinuation of Butorphanol Tartrate

Do not rapidly reduce or abruptly discontinue butorphanol tartrate in patients who may be physically dependent on opioids. Rapid reduction or abrupt discontinuation of opioid analgesics in patients who are physically dependent on opioids has resulted in serious withdrawal symptoms, uncontrolled pain, and suicide. Rapid reduction or abrupt discontinuation has also been associated with attempts to find other sources of opioid analgesics, which may be confused with drug-seeking for abuse. Patients may also attempt to treat their pain or withdrawal symptoms with illicit opioids, such as heroin, and other substances.

When a decision has been made to decrease the dose or discontinue therapy in an opioid-dependent patient taking butorphanol tartrate nasal spray, there are a variety of factors that should be considered, including the total daily dose of opioid (including butorphanol tartrate nasal spray) the patient has been taking, the duration of treatment, the type of pain being treated, and the physical and psychological attributes of the patient. It is important to ensure ongoing care of the patient and to agree on an appropriate tapering schedule and follow-up plan so that patient and provider goals and expectations are clear and realistic. When opioid analgesics are being discontinued due to a suspected substance use disorder, evaluate and treat the patient, or refer for evaluation and treatment of the substance use disorder. Treatment should include evidence-based approaches, such as medication assisted treatment of opioid use disorder. Complex patients with co-morbid pain and substance use disorders may benefit from referral to a specialist.

There are no standard opioid tapering schedules that are suitable for all patients. Good clinical practice dictates a patient-specific plan to taper the dose of the opioid gradually. For patients on butorphanol tartrate nasal spray who are physically opioid-dependent, initiate the taper by a small enough increment (e.g., no greater than 10% to 25% of the total daily dose) to avoid withdrawal symptoms, and proceed with dose lowering at an interval of every 2 to 4 weeks. Patients who have been taking opioids for briefer periods of time may tolerate a more rapid taper.

It may be necessary to provide the patient with lower dosage strengths to accomplish a successful taper. Reassess the patient frequently to manage pain and withdrawal symptoms, should they emerge. Common withdrawal symptoms include restlessness, lacrimation, rhinorrhea, yawning, perspiration, chills, myalgia, and mydriasis. Other signs and symptoms also may develop, including irritability, anxiety, backache, joint pain, weakness, abdominal cramps, insomnia, nausea, anorexia, vomiting, diarrhea, or increased blood pressure, respiratory rate, or heart rate. If withdrawal symptoms arise, it may be necessary to pause the taper for a period of time or raise the dose of the opioid analgesic to the previous dose, and then proceed with a slower taper. In addition, evaluate patients for any changes in mood, emergence of suicidal thoughts, or use of other substances.

When managing patients taking opioid analgesics, particularly those who have been treated for an extended period of time, and/or with high doses for chronic pain, ensure that a multimodal approach to pain management, including mental health support (if needed), is in place prior to initiating an opioid analgesic taper. A multimodal approach to pain management may optimize the treatment of chronic pain, as well as assist with the successful tapering of the opioid analgesic [see WARNINGS/ Withdrawal, DRUG ABUSE AND DEPENDENCE].

Safety and Handling

Butorphanol tartrate nasal spray is an open delivery system with increased risk of exposure to healthcare workers.

In the priming process, a certain amount of butorphanol may be aerosolized; therefore, the pump sprayer should be aimed away from the patient or other people or animals.

The disposal of Schedule IV controlled substances must be consistent with State and Federal Regulations. The unit should be disposed of by unscrewing the cap, rinsing the bottle, and placing the parts in a waste container.

HOW SUPPLIED

Butorphanol tartrate nasal spray, USP is supplied in a child-resistant plastic container containing a 2.5 mL bottle of nasal spray solution (10 mg/mL) and a metered-dose spray pump with protective clip and dust cover, a bottle of nasal spray solution, and a patient instruction leaflet and medication guide. On average, one bottle will deliver 14 to 15 doses if no repriming is necessary.

Butorphanol Tartrate Nasal Spray USP, 10 mg/mL

NDC 60505-0813-1 - 10 mg per mL, 2.5 mL bottle

Storage Conditions

Store at 20°C to 25°C (68°F to 77°F) [see USP Controlled Room Temperature].

Store butorphanol tartrate nasal spray securely and dispose of properly [see PRECAUTIONS/ Information for Patients].

^1IMITREX® is a registered trademark of Glaxo-Wellcome, Inc.

PHARMACIST ASSEMBLY INSTRUCTIONS FOR BUTORPHANOL TARTRATE NASAL SPRAY, USP

The pharmacist will assemble butorphanol tartrate nasal spray prior to dispensing to the patient, according to the following instructions:

1. Open the child-resistant plastic container and remove the spray pump and solution bottle.

2. Assemble butorphanol tartrate nasal spray by first unscrewing the white cap from the solution bottle and screwing the pump unit tightly onto the bottle. Make sure the clear cover is on the pump unit.

3. Return the butorphanol tartrate nasal spray bottle to the child-resistant plastic container for dispensing to the patient with patient instruction leaflet and medication guide.

APOTEX INC.
BUTORPHANOL TARTRATE NASAL SPRAY, USP
10 mg/mL

Manufactured by | Manufactured for
Apotex Inc. | Apotex Corp.
Toronto, Ontario | Weston, FL
Canada M9L 1T9 | 33326

Revised: December 2025

PATIENT INSTRUCTIONS

for Butorphanol Tartrate (bue-TOR-fa-nol TAR-trate) Nasal Spray, USP 10 mg/mL

PATIENT INSTRUCTIONS

Take medication as directed by your physician. For proper use of the nasal spray, read the following instructions carefully.

NOTE: BOTTLES DO NOT APPEAR "FULL". THEY ARE PRE-FILLED TO DELIVER ON AVERAGE 14 TO 15 ONE (1) MG DOSES. (THE USUAL DOSE IS 1 MG-ONE SPRAY IN ONE NOSTRIL.)

THE UNIT MUST BE PRIMED WITH ONE OR TWO STROKES IF NOT USED FOR 48 HOURS OR LONGER.

Note: With intermittent use requiring repriming before each dose, the 2.5 mL bottle will deliver an average of 8 to 10 doses of butorphanol tartrate nasal spray.

When not in use, store spray unit in child-resistant container. Butorphanol tartrate nasal spray should not be used by anyone other than the person for whom it was prescribed. To prevent this, and to reduce the chance of children taking the drug it is important to dispose of any excess butorphanol tartrate nasal spray just as soon as it is no longer needed.

The best way to safely dispose of the unit is to unscrew the cap, rinse the bottle and spray assembly under the water faucet, and dispose of the parts in a waste can where children cannot easily get to them.

Figure 1

1. Blow nose gently to clear both nostrils.

Figure 2

2. Pull clear cover off pump unit. Remove protective clip from neck of pump unit.

Figure 3

3. Prime butorphanol tartrate nasal spray by placing nozzle between first and second finger with thumb on the bottom of bottle. Pump sprayer unit FIRMLY and QUICKLY until a fine spray appears (up to 7 to 8 strokes).

Figure 4

4. Insert spray tip approximately 1 cm (width of small finger) into one nostril, pointing the tip toward the back of the nose.

Figure 5

5. Close other nostril with your forefinger and tilt head slightly forward.

Figure 6

6. Pump spray unit firmly and quickly by pushing down on the "finger grips" of the pump unit and against the thumb at the bottom of the bottle. Sniff gently with your mouth closed.

Figure 7

7. After spraying, remove pump unit from nose. Tilt your head backwards and sniff gently a few more seconds.

8. Your doctor will tell you whether a two-spray dose is needed. If needed, administer a second spray in the other nostril, following steps 4 through 7. Replace protective clip and clear cover, respectively, (Fig. 2) after each dose.

USUAL DOSE: ONE Spray. Spray ONLY ONCE into ONLY ONE nostril.
DO NOT spray into both nostrils unless directed by your doctor.
DO NOT repeat sooner than directed by your doctor.

APOTEX INC.
BUTORPHANOL TARTRATE NASAL SPRAY, USP
10 mg/mL

Manufactured by
Apotex Inc.
Toronto, Ontario
Canada M9L 1T9

Manufactured for
Apotex Corp.
Weston, FL
33326

Revised: December 2025

MEDICATION GUIDE

Butorphanol Tartrate (bue-TOR-fa-nol TAR-trate) Nasal Spray, USP 10 mg/mL

Butorphanol tartrate nasal spray is:

- A strong prescription pain medicine that contains an opioid (narcotic) that is used to manage pain when other pain treatments such as non-opioid pain medicines do not treat your pain well enough or you cannot tolerate them.
- An opioid pain medicine that can put you at risk for overdose and death. Even if you take your dose correctly as prescribed you are at risk for opioid addiction, abuse, and misuse that can lead to death.

Important information about butorphanol tartrate nasal spray:

- Get emergency help or call 911 right away if you take too much butorphanol tartrate nasal spray (overdose). When you first start taking butorphanol tartrate nasal spray, when your dose is changed, or if you take too much (overdose), serious or life-threatening breathing problems that can lead to death may occur. Ask your healthcare provider about medicines like naloxone or nalmefene that can be used in an emergency to reverse an opioid overdose.
- Taking butorphanol tartrate nasal spray with other opioid medicines, benzodiazepines, gabapentinoids (gabapentin or pregabalin), alcohol, or other central nervous system depressants (including street drugs) can cause severe drowsiness, decreased awareness, breathing problems, coma and death.
- Never give anyone else your butorphanol tartrate nasal spray. They could die from taking it. Store butorphanol tartrate nasal spray away from children and in a safe place to prevent stealing or abuse. Selling or giving away butorphanol tartrate nasal spray is against the law.
- Never give anyone else your butorphanol tartrate nasal spray. They could die from taking it. Selling or giving away butorphanol tartrate nasal spray is against the law.
- Store butorphanol tartrate nasal spray securely, out of sight and reach of children, and in a location not accessible by others, including visitors to the home.

Do not take butorphanol tartrate nasal spray if you have:

- Severe asthma, trouble breathing, or other lung problems.
- A bowel blockage or have narrowing of the stomach or intestines.
- Previously had an allergic reaction to butorphanol or the preservative benzethonium chloride.

Before taking butorphanol tartrate nasal spray, tell your healthcare provider if you have a history of:

- head injury, seizures
- liver, kidney, thyroid problems
- problems urinating
- pancreas or gallbladder problems
- abuse of street or prescription drugs, alcohol addiction, opioid overdose, or mental health problems.

Tell your healthcare provider if you are:

- noticing your pain getting worse. If your pain gets worse after you take butorphanol tartrate nasal spray, do not take more of butorphanol tartrate nasal spray without first talking to your healthcare provider. Talk to your healthcare provider if the pain that you have increases, if you feel more sensitive to pain, or if you have new pain after taking butorphanol tartrate nasal spray.
- Pregnant or planning to become pregnant. Use of butorphanol tartrate nasal spray for an extended period of time during pregnancy can cause withdrawal symptoms in your newborn baby that could be life-threatening if not recognized and treated.
- Breastfeeding. Butorphanol tartrate nasal spray passes into breast milk and may harm your baby. Carefully observe infants for increased sleepiness (more than usual), breathing difficulties, or limpness. Seek immediate medical care if you notice these signs.
- Living in a household where there are small children or someone who has abused street or prescription drugs
- Taking prescription or over-the-counter medicines, vitamins, or herbal supplements. Taking butorphanol tartrate nasal spray with certain other medicines can cause serious side effects that could lead to death.

When taking butorphanol tartrate nasal spray:

- Do not change your dose. Take butorphanol tartrate nasal spray exactly as prescribed by your healthcare provider.
- For acute (short-term) pain, you may only need to take butorphanol tartrate nasal spray for a few days. You may have some butorphanol tartrate nasal spray left over that you did not use. See disposal information at the bottom of this section for directions on how to safely throw away (dispose of) your unused butorphanol tartrate nasal spray.
- See the detailed Patient Instructions for information about how to take butorphanol tartrate nasal spray. Use the lowest dose possible for the shortest time needed.
- Take your prescribed dose as instructed by your healthcare provider as needed for pain. Do not take more than your prescribed dose. If you miss a dose, take your next dose at your usual time.
- Call your healthcare provider if the dose you are taking does not control your pain.
- If you have been taking butorphanol tartrate nasal spray regularly, do not stop taking butorphanol tartrate nasal spray without talking to your healthcare provider.
- After you stop taking butorphanol tartrate nasal spray, dispose of unused butorphanol tartrate nasal spray by unscrewing the cap, rinsing the bottle, and placing the parts in a waste container.
- After you stop taking Butorphanol Tartrate Nasal Spray, dispose of unused Butorphanol Tartrate Nasal Spray by unscrewing the cap, rinsing the bottle, and placing the parts in a waste container. Visit www.fda.gov/drugdisposal for additional information on disposal of unused medicines.

While taking butorphanol tartrate nasal spray DO NOT:

- Drive or operate heavy machinery, until you know how butorphanol tartrate nasal spray affects you. Butorphanol tartrate nasal spray can make you sleepy, dizzy, or lightheaded.
- Drink alcohol or use prescription or over-the-counter medicines that contain alcohol. Using products containing alcohol during treatment with butorphanol tartrate nasal spray may cause you to overdose and die.

The possible side effects of butorphanol tartrate nasal spray:

- Constipation, nausea, sleepiness, vomiting, tiredness, headache, dizziness, abdominal pain. Call your healthcare provider if you have any of these symptoms and they are severe.
- Trouble breathing. Taking butorphanol tartrate nasal spray with other opioid medicines, benzodiazepines, gabapentinoids (gabapentin or pregabalin), alcohol, or other central nervous system depressants (including street drugs) can cause breathing problems that can lead to coma and death.

Get emergency medical help or call 911 right away if you have:

- trouble breathing, shortness of breath, fast heartbeat, chest pain, swelling of your face, tongue, or throat, extreme drowsiness, light-headedness when changing positions, feeling faint, agitation, high body temperature, trouble walking, stiff muscles, or mental changes such as confusion.

These are not all the possible side effects of butorphanol tartrate nasal spray. Call your healthcare provider for medical advice about side effects. You may report side effects to FDA at 1-800-FDA-1088. For more information go to dailymed.nlm.nih.gov

This Medication Guide has been approved by the U.S. Food and Drug Administration.

KEEP OUT OF THE REACH OF CHILDREN.

APOTEX INC.
BUTORPHANOL TARTRATE NASAL SPRAY, USP
10 mg/mL

Manufactured by | Manufactured for
Apotex Inc. | Apotex Corp.
Toronto, Ontario | Weston, FL
Canada M9L 1T9 | 33326

Revised: December 2025

PACKAGE LABEL

PACKAGE LABEL - PRINCIPAL DISPLAY PANEL - 2.5 ML LABEL

APOTEX CORP. NDC 60505-0813-1

CIV

Butorphanol Tartrate Nasal Spray, USP - For Nasal Use Only

10mg/mL

Rx only